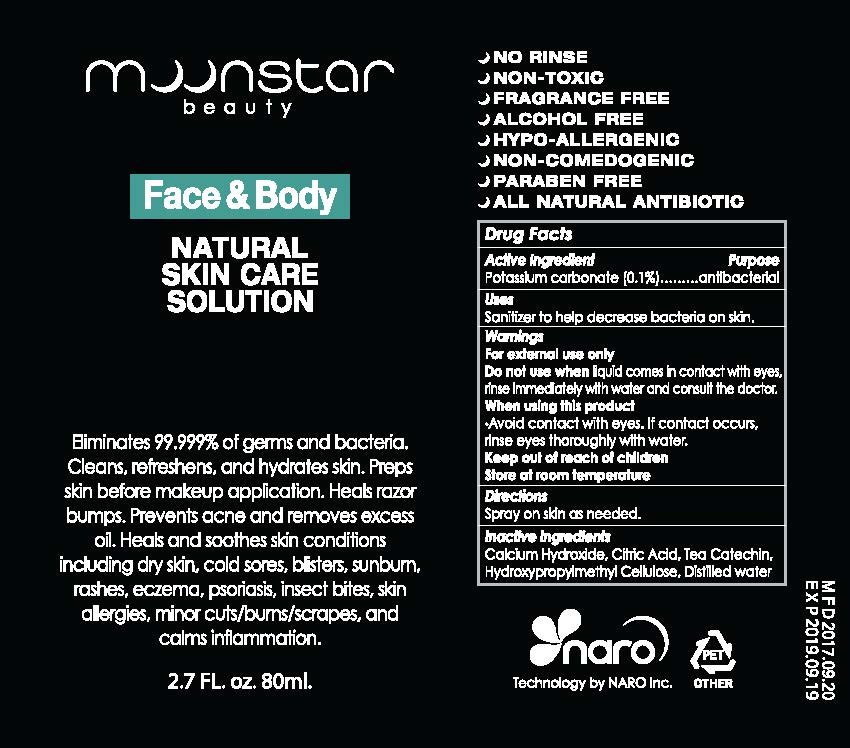 DRUG LABEL: FACE-BODY-S
NDC: 71957-0003 | Form: LIQUID
Manufacturer: NARO, INC.
Category: otc | Type: HUMAN OTC DRUG LABEL
Date: 20180101

ACTIVE INGREDIENTS: POTASSIUM CARBONATE 0.1 g/100 mL
INACTIVE INGREDIENTS: WATER

ACTIVE INGREDIENT

Potassium carbonate

INACTIVE INGREDIENT

Water, etc

PURPOSE

Antibacterial

Keep out of reach of children

INDICATIONS AND USAGE

Spray on skin as needed

WARNINGS

For external use only
Do not use when liquid comes in contact with eyes, rinse immediately with water and consult the doctor.
When using this product

- Do not apply on other parts of the body
- Avoid contact with eyes. If contact occurs, rinse eyes thoroughly with water.

Store at room temperature

DOSAGE AND ADMINISTRATION

For external use only